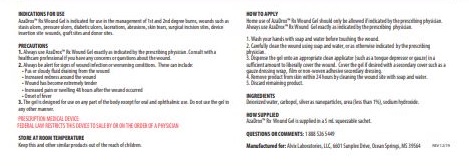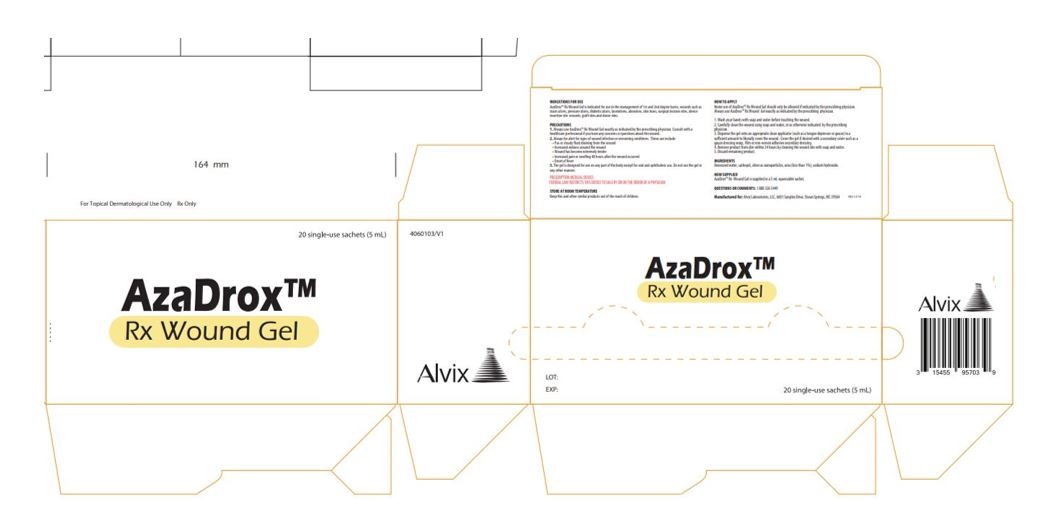 DRUG LABEL: AzaDrox Rx Wound Gel
NDC: 00315455957039
Manufacturer: Alvix Laboratories, LLC
Category: other | Type: PRESCRIPTION MEDICAL DEVICE LABEL
Date: 20200518

AzaDrox Rx Wound Gel

DESCRIPTION

AzaDrox™ Rx Wound Gel is a wound dressing hydrogel that helps maintain a moist wound environment that is conducive to healing by either absorbing or donating moisture and wound exudates.

INDICATIONS FOR USE

AzaDrox™ Rx Wound Gel is indicated for use in the management of 1st and 2nd degree burns, wounds such as stasis ulcers, pressure ulcers, diabetic ulcers, lacerations, abrasions, skin tears, surgical incision sites, device insertion site wounds, graft sites and donor sites.

PRECAUTIONS

1. Always use AzaDrox™ Rx Wound Gel exactly as indicated by the prescribing physician. Consult with a healthcare professional if you have any concerns or questions about the wound.

2. Always be alert for signs of wound infection or worsening conditions. These can include:

• Pus or cloudy fluid draining from the wound
• Increased redness around the wound
• Wound has become extremely tender
• Increased pain or swelling 48 hours after wound occurred
• Onset of fever

3. The gel is designed for use on any part of the body except for oral and opthalmic use. Do not use the gel in any other manner.

HOW TO APPLY

Home use of AzaDrox™ Rx Wound Gel should only be allowed if indicated by the prescribing physician. Always use AzaDrox™ Rx Wound Gel exactly as indicated by the prescribing physician.

1. Wash your hands with soap and water before touching the wound.

2. Carefully clean the wound using soap and water, or as otherwise indicated by the prescribing physician.

3. Dispense gel onto appropriate clean applicator (such as a tongue depressor or gauze) in a sufficient amount to liberally cover the wound. Cover the gel if desired with a secondary cover such as a gauze dressing wrap, film, or non-woven adhesive secondary dressing.

4. Remove product from the skin within 24 hours by leaning the wound site with soap and water.

5. Discard remaining product.

INGREDIENTS

Deionized water, carbopol, silver as nanoparticles, urea (less than 1%), sodium hydroxide

HOW SUPPLIED

AzaDrox™ Rx Wound Gel is supplied in a carton containing 20 single-use 5 mL sachets. 1545595703 (GTIN: 00315455957039)

PRESCRIPTION MEDICAL DEVICE: FEDERAL LAW RESTRICTS THIS DEVICE TO SALE BY OR ON THE ORDER OF A PHYSICIAN

STORE AT ROOM TEMPERATURE

Keep this and other similar products out of the reach of children.

Alvix Laboratories, LLC

Ocean Springs, MS 39564

1 888 526 5449